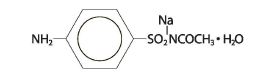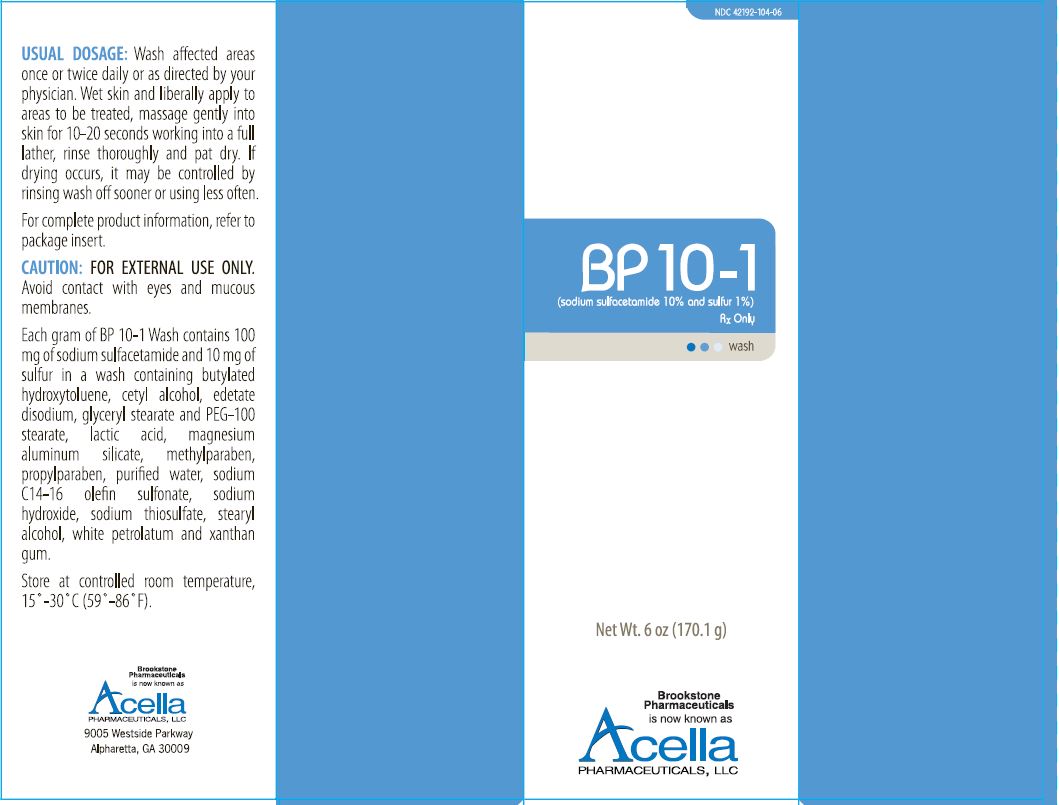 DRUG LABEL: SODIUM SULFACETAMIDE and SULFUR


NDC: 42192-104 | Form: LIQUID
Manufacturer: Acella Pharmaceuticals, LLC
Category: prescription | Type: HUMAN PRESCRIPTION DRUG LABEL
Date: 20240108

ACTIVE INGREDIENTS: SULFACETAMIDE SODIUM 100 mg/1 g; SULFUR 10 mg/1 g
INACTIVE INGREDIENTS: BUTYLATED HYDROXYTOLUENE; CETYL ALCOHOL; EDETATE DISODIUM; GLYCERYL MONOSTEARATE; PEG-100 STEARATE; LACTIC ACID; MAGNESIUM ALUMINUM SILICATE; METHYLPARABEN; PROPYLPARABEN; WATER; SODIUM C14-16 OLEFIN SULFONATE; SODIUM HYDROXIDE; SODIUM THIOSULFATE; STEARYL ALCOHOL; PETROLATUM; XANTHAN GUM

BP10-1
(sodium sulfacetamide 10% and sulfur 1 %)
wash
RxOnly

DESCRIPTION

DESCRIPTION:Each gram of BP 10-1 Wash contains 100 mg of sodium sulfacetamide and 10 mg of sulfur in a wash containing butylated hydroxytoluene, cetyl alcohol, edetate disodium, glyceryl stearate and PEG-100 stearate, lactic acid, magnesium aluminum silicate, methylparaben, propylparaben, purified water, sodium C14-16 olefin sulfonate, sodium hydroxide, sodium thiosulfate, stearyl alcohol, white petrolatum, and xanthan gum.

Sodium sulfacetamide is a sulfonamide with antibacterial activity while sulfur acts as a keratolytic agent. Chemically, sodium sulfacetamide is N-[(4- aminophenyl) sulfonyl]acetamide, monosodium salt monohydrate.

The structural formula is:

CLINICAL PHARMACOLOGY

CLINICAL PHARMACOLOGY:The most widely accepted mechanism of action of sulfonamides is the Woods-Fildes theory which is based on the fact that sulfonamides act as competitive antagonists to para-aminobenzoic acid (PABA), an essential component for bacterial growth. While absorption through intact skin has not been determined, sodium sulfacetamide is readily absorbed from the gastrointestinal tract when taken orally and excreted in the urine, largely unchanged. The biological half-life has variously been reported as 7 to 12.8 hours.

The exact mode of action of sulfur in the treatment of acne is unknown, but it has been reported that it inhibits the growth of Propionibacterium acnes and the formation of free fatty acids.

INDICATIONS AND USAGE:BP 10-1 Wash is indicated in the topical control of acne vulgaris, acne rosacea and seborrheic dermatitis.

CONTRAINDICATIONS

CONTRAINDICATIONS:BP 10-1 Wash is contraindicated for use by patients having known hypersensitivity to sulfonamides, sulfur or any other component of this preparation. BP 10-1 Wash is not to be used by patients with kidney disease.

WARNINGS AND PRECAUTIONS

WARNINGS:Sensitivity to sodium sulfacetamide may occur, although it is rare. Therefore, caution and careful supervision should be observed when prescribing this drug for patients who may be prone to hypersensitivity to topical sulfonamides. Systemic toxic reactions such as agranulocytosis, acute hemolytic anemia, purpura hemorrhagica, drug fever, jaundice, and contact dermatitis indicate hypersensitivity to sulfonamides. Particular caution should be employed if areas of denuded or abraded skin are involved. FOR EXTERNAL USE ONLY. Keep away from eyes. Keep out of reach of children. Keep tube tightly closed.

PRECAUTIONS

PRECAUTIONS:General - if irritation occurs, discontinue use of the product and institute appropriate therapy. Patients should be carefully observed for possible local irritation or sensitization during long-term therapy. The object of this therapy is to achieve desquamation without irritation, but sodium sulfacetamide and sulfur can cause reddening and scaling of the epidermis. These side effects are not unusual in the treatment of acne vulgaris, but patients should be cautioned about the possibility.

CARCINOGENESIS AND MUTAGENESIS AND IMPAIRMENT OF FERTILITY

Carcinogenesis, Mutagenesis and Impairment of Fertility -Long-term studies in animals have not been performed to evaluate carcinogenic potential.

PREGNANCY

Pregnancy -Category C. Animal reproduction studies have not been conducted with BP 10-1 Wash. It is also not known whether BP 10-1 Wash can cause fetal harm when administered to a pregnant woman or can affect reproduction capacity. BP 10-1 Wash should be given to a pregnant woman only if clearly needed.

NURSING MOTHERS

Nursing Mothers -It is not known whether sodium sulfacetamide is excreted in human milk following topical use of BP 10-1 Wash. However, small amounts of orally administered sulfonamides have been reported to be eliminated in human milk. In view of this and because many drugs are excreted in human milk, caution should be exercised when BP 10-1 Wash is administered to a nursing woman.

PEDIATRIC USE

Pediatric Use -Safety and effectiveness in children under the age of 12 have not been established.

ADVERSE REACTIONS

ADVERSE REACTIONS:Although rare, sodium sulfacetamide may cause local irritation.

DOSAGE AND ADMINISTRATION:Wash affected areas once or twice daily, or as directed by your physician. Avoid contact with eyes or mucous membranes. Wet skin and liberally apply to areas to be treated, massage gently into skin for 10-20 seconds working into a full lather, rinse thoroughly and pat dry. If drying occurs, it may be controlled by rinsing wash off sooner or using less often.

HOW SUPPLIED

HOW SUPPLIED:BP 10-1 Wash is available in 170.1 g (6.0 oz) tubes, NDC 42192-104-06. Store at controlled room temperature, 15°-30°C (59°-86°F).

PACKAGE LABEL.PRINCIPAL DISPLAY - 170 g carton

NDC 42192-104-06

BP 10-1
(sodium sulfocetamide 10% and sulfur 1%)
RxOnly
wash

Net Wt. 6 oz (170.1 g)

Brookstone
Pharmaceuticals
is now known as
Acella
PHARMACEUTICALS, LLC